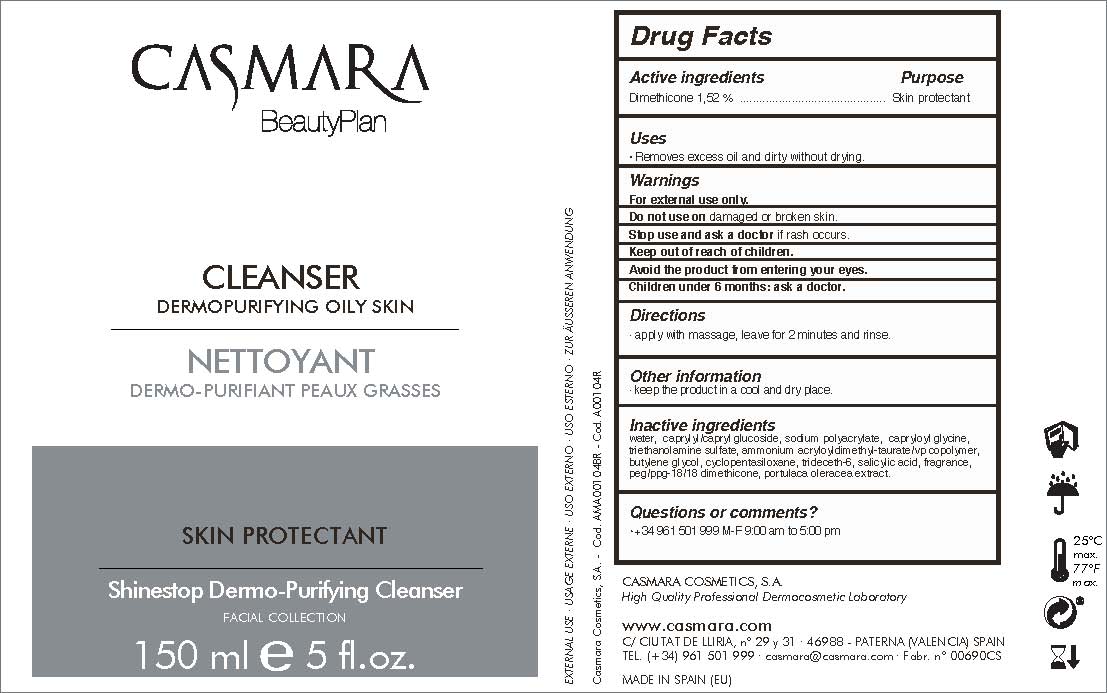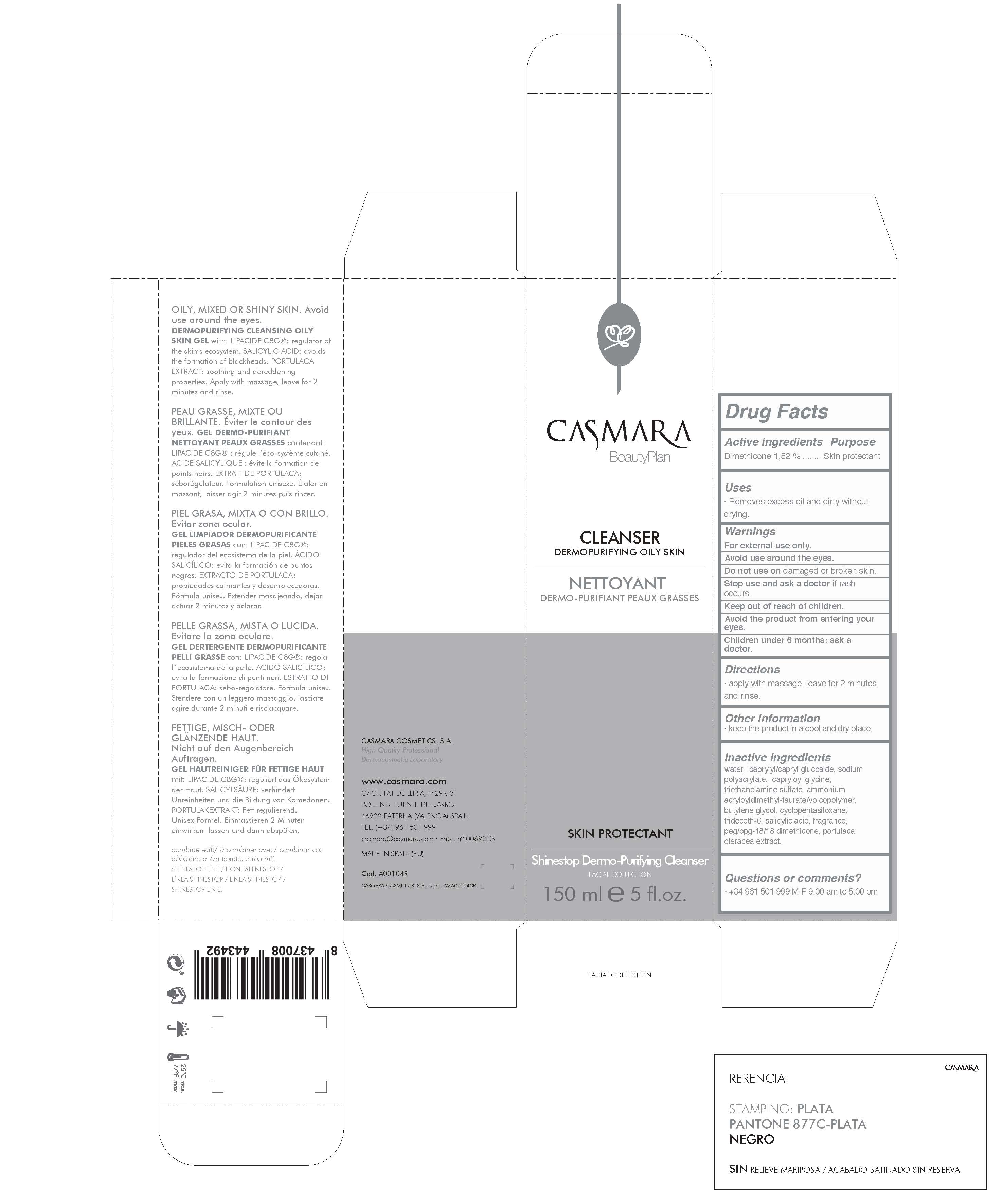 DRUG LABEL: Cleanser Dermopurifying Oily Skin
NDC: 20151-073 | Form: LIQUID
Manufacturer: Casmara Cosmetics, SA
Category: otc | Type: HUMAN OTC DRUG LABEL
Date: 20161101

ACTIVE INGREDIENTS: DIMETHICONE 1.52 mg/1 mL
INACTIVE INGREDIENTS: CAPRYLYL GLUCOSIDE 6 mg/1 mL; HYDROXYETHYL ACRYLATE/SODIUM ACRYLOYLDIMETHYL TAURATE COPOLYMER (45000 MPA.S AT 1%) 1 mg/1 mL; BUTYLENE GLYCOL 0.9 mg/1 mL; PORTULACA OLERACEA SEED 0.012 mg/1 mL; SALICYLIC ACID 0.2 mg/1 mL; CAPRYLOYL GLYCINE 2 mg/1 mL; TRIETHANOLAMINE SULFATE 1.4 mg/1 mL; WATER 83.5 mg/1 mL; TETRASODIUM GLUTAMATE DIACETATE 0.094 mg/1 mL; SODIUM POLYACRYLATE (8000 MW) 2.08 mg/1 mL; PERFLUNAFENE 0.1 mg/1 mL; CYCLOMETHICONE 5 0.72 mg/1 mL; TRIDECETH-6 0.48 mg/1 mL; PEG/PPG-18/18 DIMETHICONE 0.08 mg/1 mL

Cleanser Dermopurifying oily. Skin Protectant Shinestop Dermo-purifying Cleanser.

WARNINGS

For external use only.

Do not use on damaged or broken skin.

Stop use and ask a doctor if rash occurs.

Keep out of reach of children.

Avoid the product from entering your eyes.

Children under 6 months: as a doctor.

Stop use and ask a doctor if rash occurs

Children under 6 months: ask a doctor

. keep out of reach of children

Questions or comments? + 34 961 501 099 M-F 9:00 am to 5:00 pm

OTHER SAFETY INFORMATION

. keep the product in a cool and dry place

Directions

. apply with massage, leave for two minutes and rinse.

DOSAGE AND ADMINISTRATION

. apply with massage, leave for two minutes and rinse

Uses

. removes excess oil and dirty without drying

INACTIVE INGREDIENT

water, capryl glucoside, sodium polyacrylate, capryloyl glycine, triethanolamine sulfate, ammonium acryloydimethyl taurate/VP copolymer, butylene glycol, cyclopentasiloxane, trideceth-6, salicylic acid, fragrance, PEG/PPG-18/18 dimethicone, portulaca oleracea extract.

PURPOSE

. removes excess oil and dirty without drying.

Active Ingredients

Dimethicone 1.52%.....................Skin Protectant

PACKAGE LABEL

Cleanser Dermopurifying Oily skin

Skin protectant

Shinestop Dermopurifying Cleanser

Facial Collection